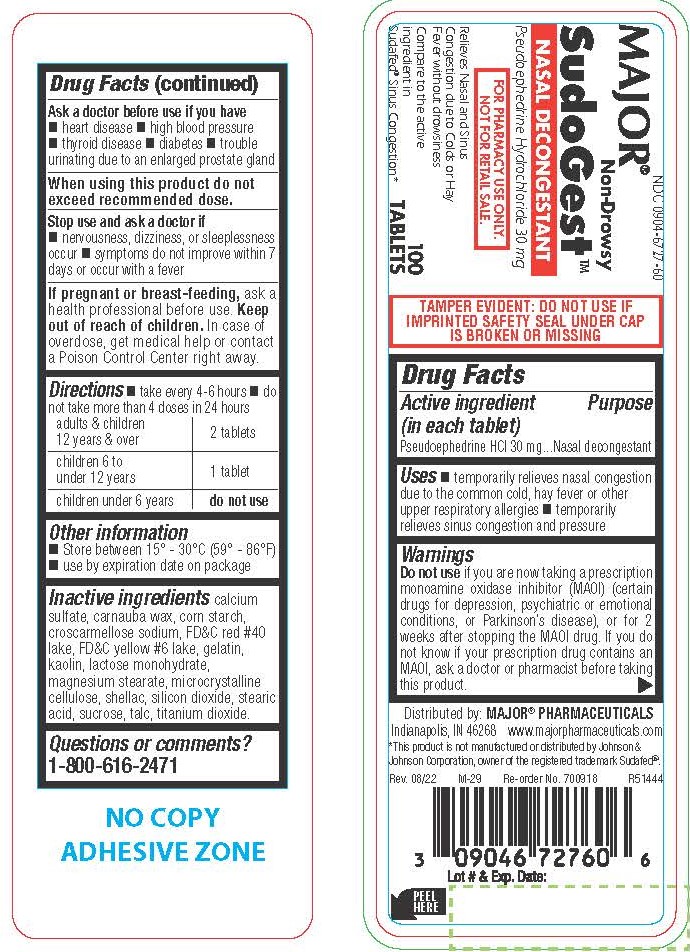 DRUG LABEL: Pseudoephedrine Hydrochloride
NDC: 0904-6727 | Form: TABLET
Manufacturer: Major Pharmaceuticals
Category: otc | Type: HUMAN OTC DRUG LABEL
Date: 20250813

ACTIVE INGREDIENTS: PSEUDOEPHEDRINE HYDROCHLORIDE 30 mg/1 1
INACTIVE INGREDIENTS: STARCH, CORN; SILICON DIOXIDE; LACTOSE MONOHYDRATE; MAGNESIUM STEARATE; MICROCRYSTALLINE CELLULOSE; TITANIUM DIOXIDE; KAOLIN; CALCIUM SULFATE ANHYDROUS; CARNAUBA WAX; CROSCARMELLOSE SODIUM; FD&C RED NO. 40; SHELLAC; STEARIC ACID; SUCROSE; FD&C YELLOW NO. 6; GELATIN; TALC

1004- Major

Drug Facts

Active ingredient (in each tablet)

Pseudoephedrine HCl 30 mg

Purpose

Nasal decongestant

Uses

- temporarily relieves nasal congestion due to the common cold, hay fever or other upper respiratory allergies
- temporarily relieves sinus congestion and pressure

WARNINGS

Do not use if you are now taking a prescription monoamine oxidase inhibitor (MAOI) (certain drugs for depression, psychiatric or emotional conditions, or Parkinson’s disease), or for 2 weeks after stopping the MAOI drug. If you do not know if your prescription drug contains an MAOI, ask a doctor or pharmacist before taking this product.

Ask a doctor before use if you have

- heart disease
- high blood pressure
- thyroid disease
- diabetes
- trouble urinating due to an enlarged prostate gland

When using this product do not exceed recommended dose.

Stop use and ask a doctor if

- nervousness, dizziness, or sleeplessness occur
- symptoms do not improve within 7 days or occur with a fever

PREGNANCY OR BREAST FEEDING

If pregnant or breast-feeding, ask a health professional before use.

Keep out of reach of children.

OVERDOSAGE

In case of overdose, get medical help or contact a Poison Control Center right away.

Directions

- take every 4-6 hours
- do not take more than 4 doses in 24 hours

adults & children 12 years & over | 2 tablets
children 6 to under 12 years | 1 tablets
children under 6 years | do not use

Other information

- Store between 15° - 30°C (59° - 86°F)
- use by expiration date on package

INACTIVE INGREDIENT

calcium sulfate, carnauba wax, corn starch, croscarmellose sodium, FD&C red #40 lake, FD&C yellow #6 lake, gelatin, kaolin, lactose monohydrate, magnesium stearate, microcrystalline cellulose, shellac, silicon dioxide, stearic acid, sucrose, talc, titanium dioxide.

Questions or comments?

1-800-616-2471

TAMPER EVIDENT: DO NOT USE IF IMPRINTED SAFETY SEAL UNDER CAP IS BROKEN OR MISSING

Distributed by: MAJOR® PHARMACEUTICALS

Indianapolis, IN 46268 www.majorpharmaceuticals.com

*This product is not manufactured or distributed by Johnson & Johnson Corporation, owner of the registered trademark Sudafed®.

PACKAGE LABEL

MAJOR®

NDC 0904-6727-60

Non Drowsy SudoGestTM

Nasal Decongestant

Pseudoephedrine Hydrochloride 30mg

FOR PHARMACY USE ONLY.

NOT FOR RETAIL SALE.

Relieves Nasal and Sinus Congestion due to Colds or Hay Fever without drowsiness

Compare to the active ingredient in Sudafed® Sinus Congestion*

100 Tablets